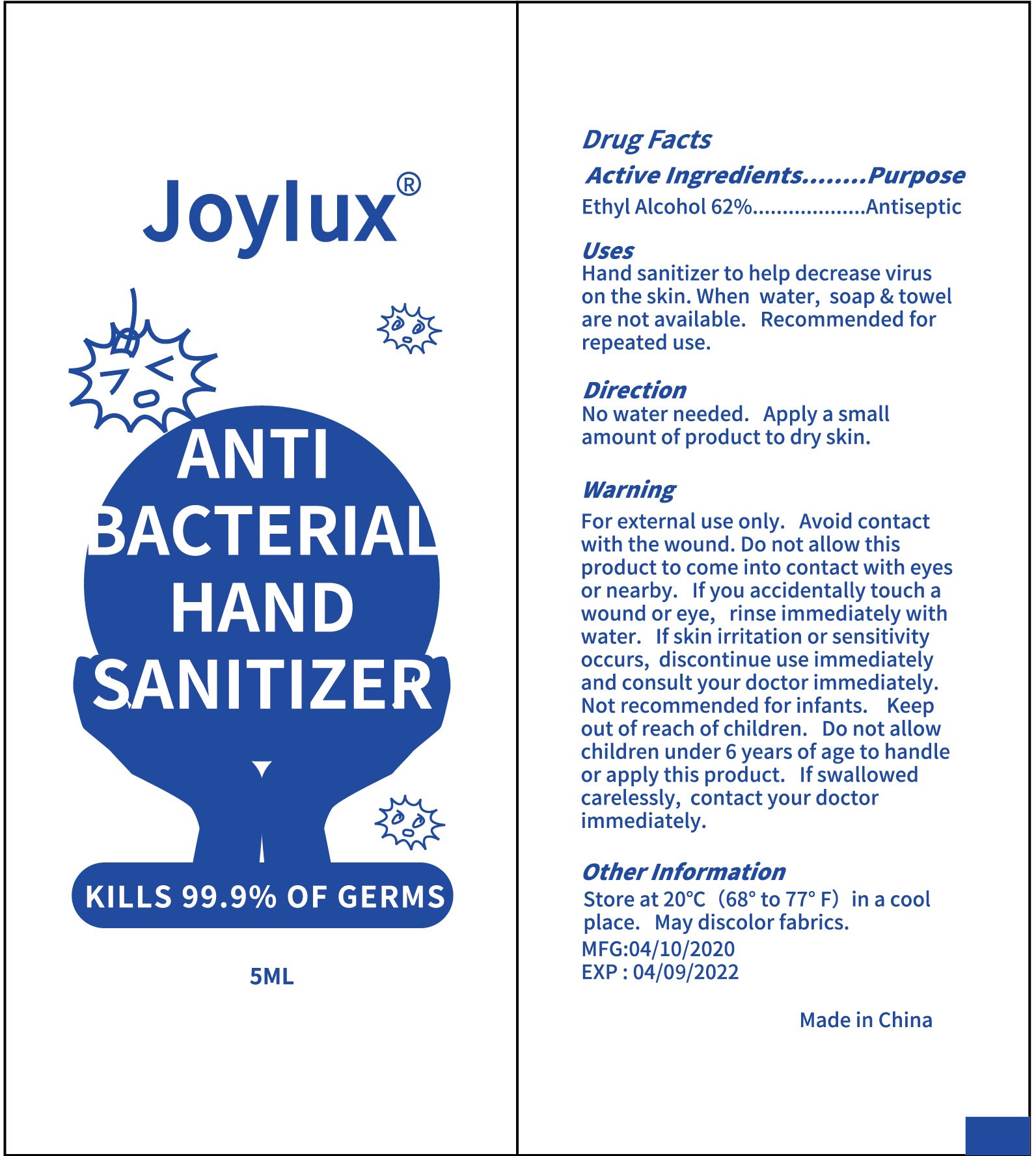 DRUG LABEL: Joylux Anti Bacterial Hand Sanitizer
NDC: 71734-301 | Form: GEL
Manufacturer: JIANGMEN SHUIZIRUN SANITARY ARTICLES CO., LTD.
Category: otc | Type: HUMAN OTC DRUG LABEL
Date: 20200428

ACTIVE INGREDIENTS: ALCOHOL 62 mL/100 mL
INACTIVE INGREDIENTS: EDETATE DISODIUM; GLYCERIN; CARBOMER 934; WATER

Drug Fact

Active Ingredient

Ethyl Alcohol 62%

Purpose

Antiseptic

Uses

Hand sanitizer to help decrease virus on the skin. When water, soap and towel are not available. Recommended for repeated use.

Warnings

For external use only.

Avoid contact with the wound.

Do not allow this produts to come into contact with eyes or nearby. If you accidentally touch a wound or eye, rinse immediately

with water. If skin irritation or sensitivity occurs, discontinue use immediately and consult your doctor.

Not recommended for infants.

When using this product

Dn not allow children under 6 years of age to handle or apply, contact your doctor immediately.

Keep out of reach of children.

If swalllowed carelessly, contact your doctor immdiately.

DOSAGE AND ADMINISTRATION

No water as needed. Apply a small amount of product to dry skin.

Inactive Ingredients

Triethanolamine, Carbomer, Glycerine, Disodium EDTA, Pure Water